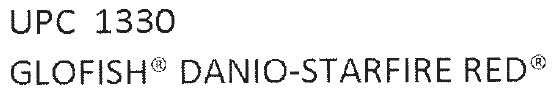 DRUG LABEL: Starfire Red Danio
NDC: 72341-014 | Form: NOT APPLICABLE
Manufacturer: GloFish LLC
Category: other | Type: Intentional Animal Genomic Alteration Label
Date: 20260211

ACTIVE INGREDIENTS: STARFIRE RED DANIO TRANSGENIC WHOLE (RZF2005 CONSTRUCTS) 1 [Amb'a'1'U]/1 [Amb'a'1'U]

GloFish®

It's GLO™ Time!

GloFish®
Experience the Glo!®

+ GloFish® are born with their beautiful, lifelong color. They are NOT injected or painted!
+ GloFish were first bred to detect water pollutants. They get their color from a fluorescence gene, similar to those found in many species of sea coral and marine fish.
+ GloFish shine brilliantly under a blue or white aquarium light!

GloFish® Fluorescent Fish License Statement

Thank you for your purchase of GloFish® fluorescent fish! Please note the following important information: 1) GloFish® fluorescent fish are intended solely for visual enjoyment as aquarium fish by end users who have purchased these fish from authorized resellers. 2) GloFish® is a trademark owned by GloFish, LLC and cannot be used in connection with the promotion or sale of any ornamental fish other than authentic GloFish® fluorescent fish, which are exclusively produced by 5-D Tropical, Inc. and Segrest Farms, Inc. 3) You agree that any bag, container, or aquarium holding GloFish® fluorescent fish for resale, other than bags provided to end users, will be marked with either "GloFish® fluorescent fish", or "GloFish®." 4) GloFish® fluorescent fish are covered under one or more of the following United States Patent Numbers: 7,834,239; 7,858,844; 7,700,825; 7,135,613; 7,442,522; 7,537,915; 7,150,979; 7,166,444; 8,153,858; 8,232,450; 8,232,451; 8,378,169; 8,581,023; 8,581,024; 8,581,025; 8,727,554; 8,975,467; 8,987,546; 9,271,478; 9,282,729; 9,295,236; 9,295,237; 9,295,238; 9,363,986; 9,374,987; 9,380,768; and 9,392,776, as well as other pending applications. 5) Intentional breeding and/or any sale, barter, or trade, of any offspring of GloFish® fluorescent fish is strictly prohibited. Please note that opening of this bag constitutes agreement to each of the foregoing points. Please see www.glofish.com/license.html for more details and send questions about this to info@glofish.com. Thank you for your cooperation!

PRINCIPAL DISPLAY PANEL - DANIO-STARFIRE RED

UPC 1330

GLOFISH® DANIO-STARFIRE RED®